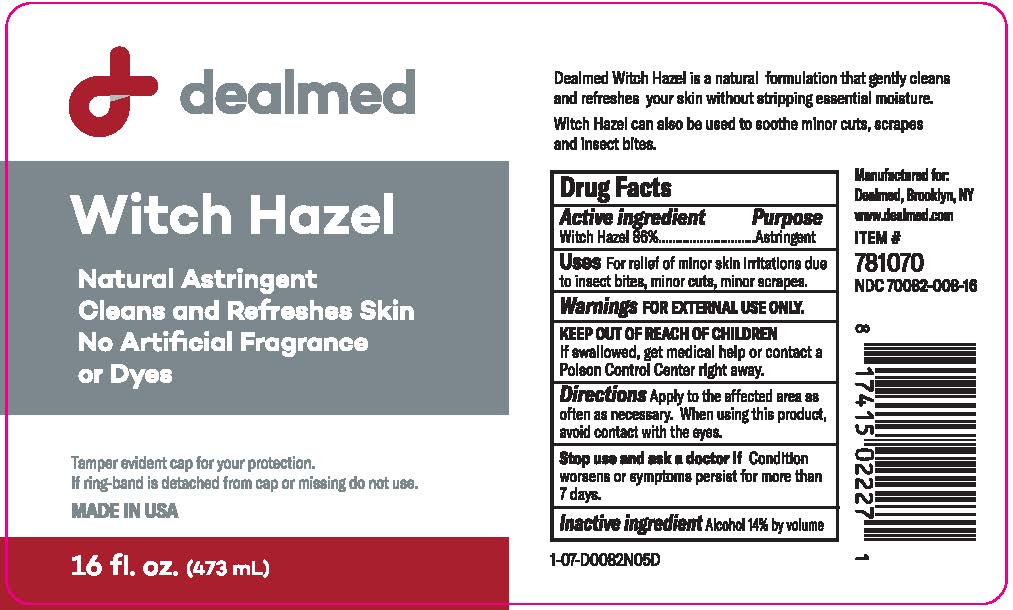 DRUG LABEL: Witch Hazel
NDC: 70082-008 | Form: LIQUID
Manufacturer: DealMed Medical Supplies LLC
Category: otc | Type: HUMAN OTC DRUG LABEL
Date: 20260112

ACTIVE INGREDIENTS: WITCH HAZEL 86 g/100 mL
INACTIVE INGREDIENTS: ALCOHOL

Witch Hazel

Active Ingredient

Witch Hazel 86%

Purpose

Astringent

Uses: Relieves minor skin irritation due to:

- insect bites
- minor cuts
- minor scrapes

Warnings

For external use only

When using this product

- Avoid contact with eyes. If contact occurs, rinse thoroughly with water.

Stop use and ask a doctor if

- Condition worsens or symptoms persist for more than 7 days.

Keep out of reach of children.

- If swallowed, get medical help or contact a Poison Control Center right away.

Directions

- After cleansing apply generously to cotton ball and gently wipe skin.
- Apply as often as needed.

Inactive ingredients

Alcohol 14% by volume.

Principal Display Panel

dealmed

Witch Hazel

Natural Astringent

Cleans and Refreshes Skin

No Artificial Fragrance

or Dyes

Tamper evident cap for your protection.

If ring-band is detached from cap or missing, do not use.

MADE IN USA

16 fl oz. (473 mL)